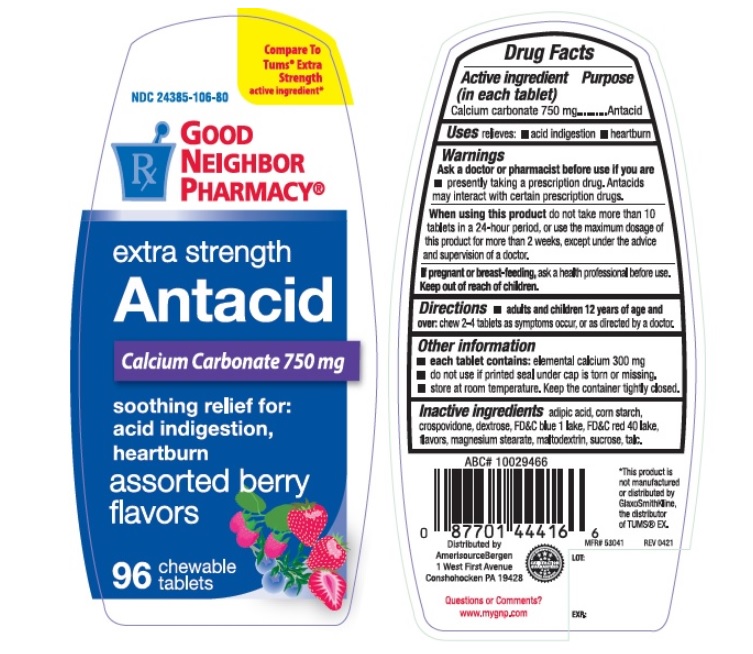 DRUG LABEL: Good Neighbor Pharmacy Antacid 
NDC: 24385-106 | Form: TABLET, CHEWABLE
Manufacturer: AmerisourceBergen Drug Corporation
Category: otc | Type: HUMAN OTC DRUG LABEL
Date: 20241226

ACTIVE INGREDIENTS: CALCIUM CARBONATE 750 mg/1 1
INACTIVE INGREDIENTS: ADIPIC ACID; STARCH, CORN; CROSPOVIDONE; DEXTROSE; FD&C BLUE NO. 1; FD&C RED NO. 40; MAGNESIUM STEARATE; MALTODEXTRIN; SUCROSE; TALC

Good Neighbor Pharmacy Antacid

Active Ingredient (in each tablet)

Calcium carbonate 750 mg

Purpose

Antacid

Uses

- relieves:
- acid indigestion
- heartburn

Warnings

Ask a doctor or pharmacist before use if you are

- presently taking a prescription drug. Antacids may interact with certain prescription drugs.

When using this product

do not take more than 10 tablets in a 24-hour period, or use the maximum dosage of this product for more than 2 weeks, except under the advice and supervision of a doctor.

If pregnant or breast-feeding, ask a health professional before use.

Keep out of reach of children.

Directions

- adults and children 12 years of age and over: chew 2-4 tablets as symptoms occur, or as directed by a doctor.

Other information

- each tablet contains: elemental calcium 300 mg
- do not use if printed seal under cap is torn or missing.
- store at room temperature. Keep the container tightly closed.

Inactive ingredients

adipic acid, corn starch, crospovidone, dextrose, FD&C blue 1 lake, FD&C red 40 lake, flavors, magnesium stearate, maltodextrin, sucrose, talc.

PDP

Good Neighbor Pharmacy Antacid

NDC 24385-106-80

Compare To Tums Extra Strength active ingredient*

extra strength

Antacid

Calcium Crabonate 750 mg

soothing relief for:

acid indigestion, heartburn

assorted berry flavors

96 chewable flavors